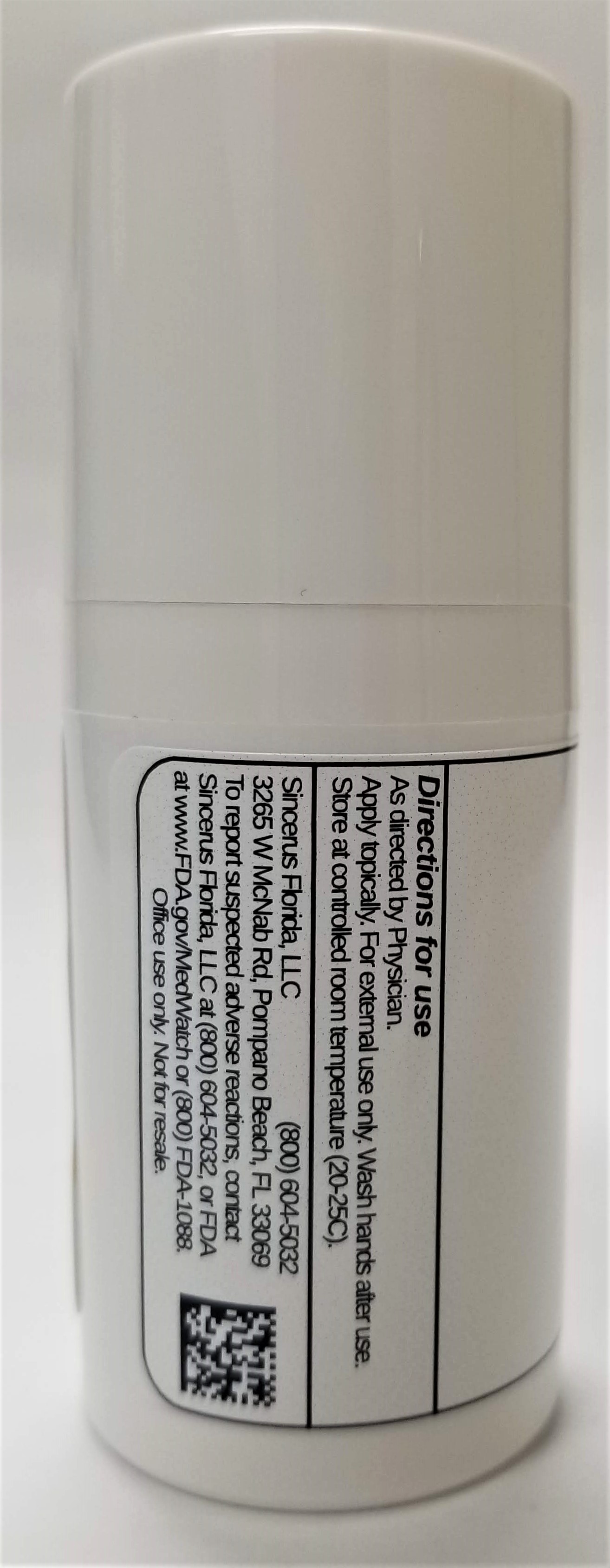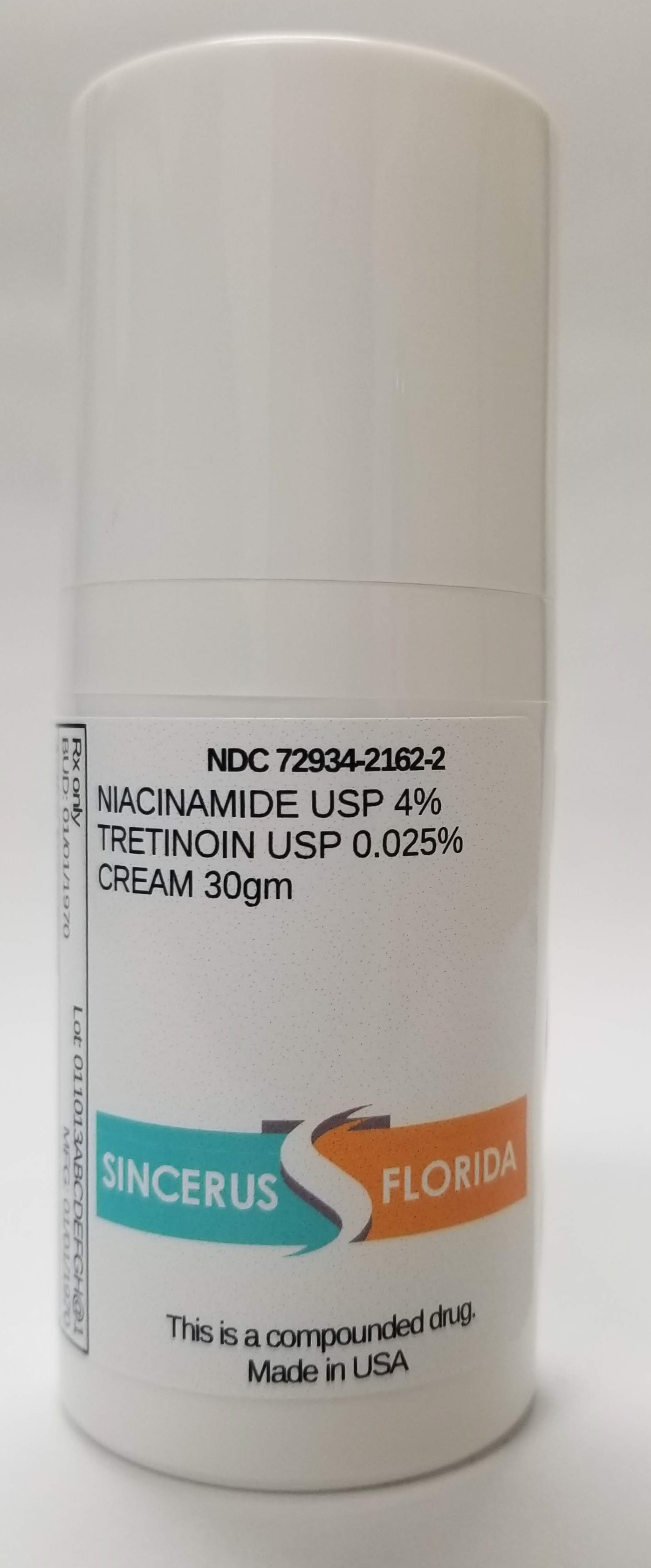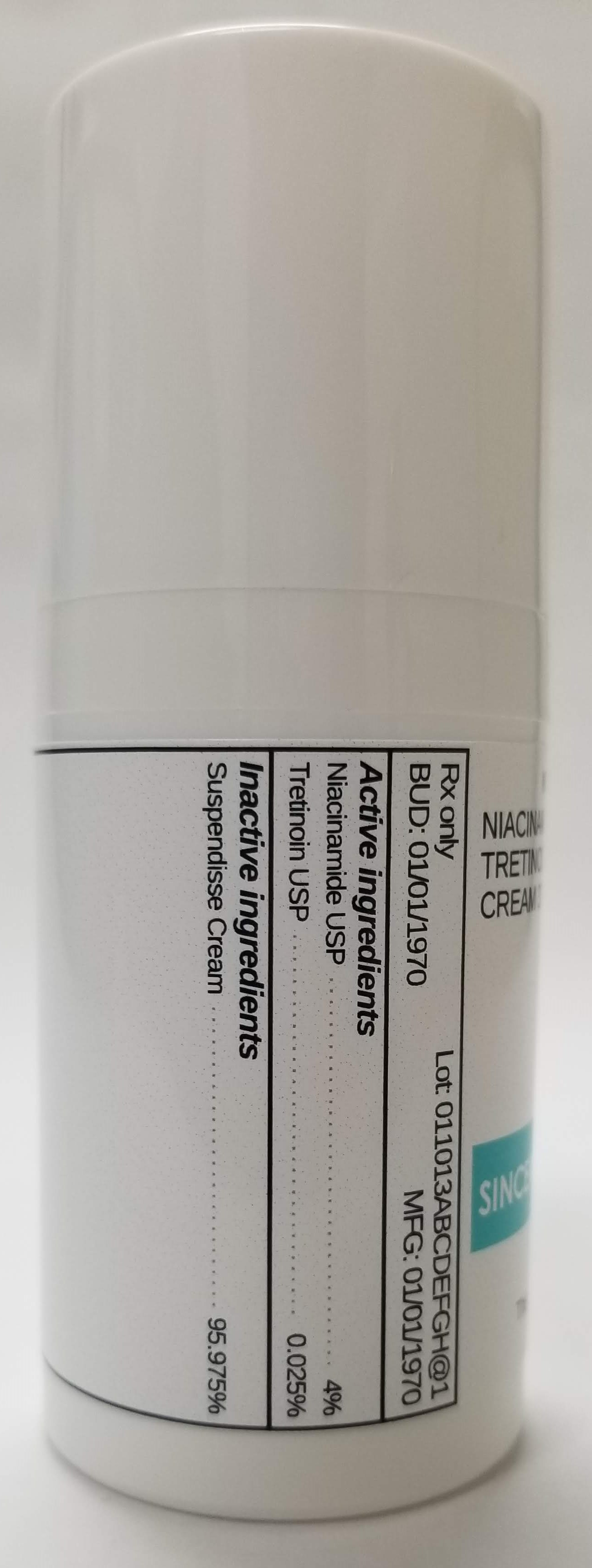 DRUG LABEL: NIACINAMIDE 4% / TRETINOIN 0.025%
NDC: 72934-2162 | Form: CREAM
Manufacturer: Sincerus Florida, LLC
Category: prescription | Type: HUMAN PRESCRIPTION DRUG LABEL
Date: 20190423

ACTIVE INGREDIENTS: TRETINOIN 0.025 g/100 g; NIACINAMIDE 4 g/100 g

NIACINAMIDE 4% / TRETINOIN 0.025%